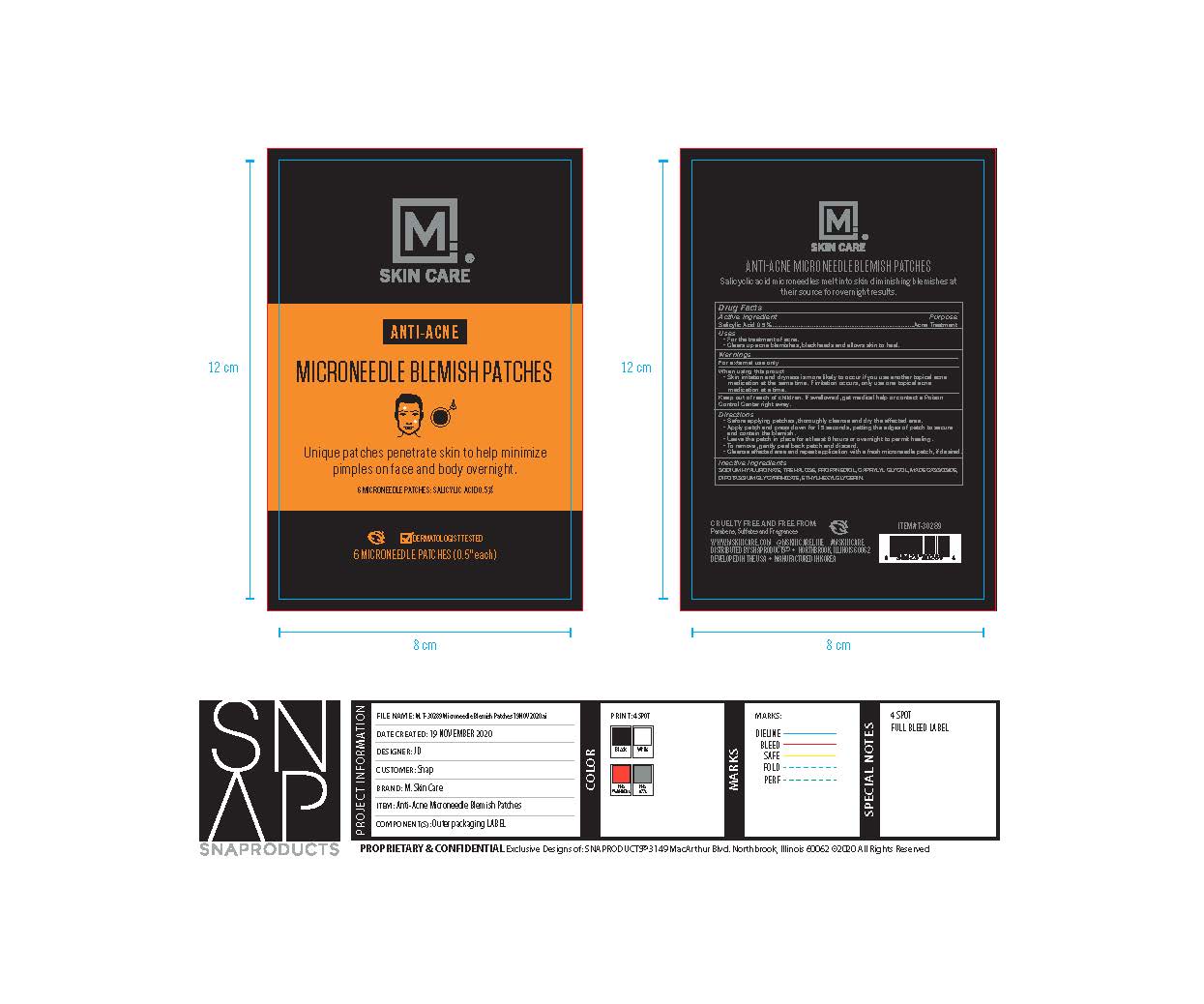 DRUG LABEL: M Skin Care Microneedle Blemish Patches
NDC: 37520-007 | Form: PATCH
Manufacturer: SALES AND PRODUCT SOLUTIONS
Category: otc | Type: HUMAN OTC DRUG LABEL
Date: 20211202

ACTIVE INGREDIENTS: SALICYLIC ACID 5 mg/1 g
INACTIVE INGREDIENTS: TREHALOSE; PROPANEDIOL; CAPRYLYL GLYCOL; MADECASSOSIDE; GLYCYRRHIZINATE DIPOTASSIUM; ETHYLHEXYLGLYCERIN; HYALURONATE SODIUM

M Skin Care Microneedle Blemish Patches

Active Ingredient

Salicylic Acid 0.5%

Purpose

Acne Treatment

Use

For the Treatment of Acne
Clears up Acne blemish, blackheads and allows skin to heal

Warnings

For external use only.

When using this product

Skin irritation and dryness is more likely to occur if you use another topical acne medication at the same time. If irritation occurs, only use one topical acne medication at a time.

Keep out of reach of children.

If swallowed, get medical help or contact a Poison Control Center right away.

Directions

- Before applying patches, thoroughly cleanse and dry the affected area
- Apply patch and press down for 15 seconds, patting the edges of patch to secure and contain the blemish.
- Leave the patch in place for at least 6 hours or overnight to permit healing
- To remove, gently peel back and discard
- Cleanse affected area and repeat application with a fresh blemish patch, if desired.

Inactive Ingredients

Sodium Hyaluronate, Trehalose, Propanediol, Caprylyl Glycol, Madecassoside, Dipotassium Glycyrrhizate, Ethylhexylglycerin